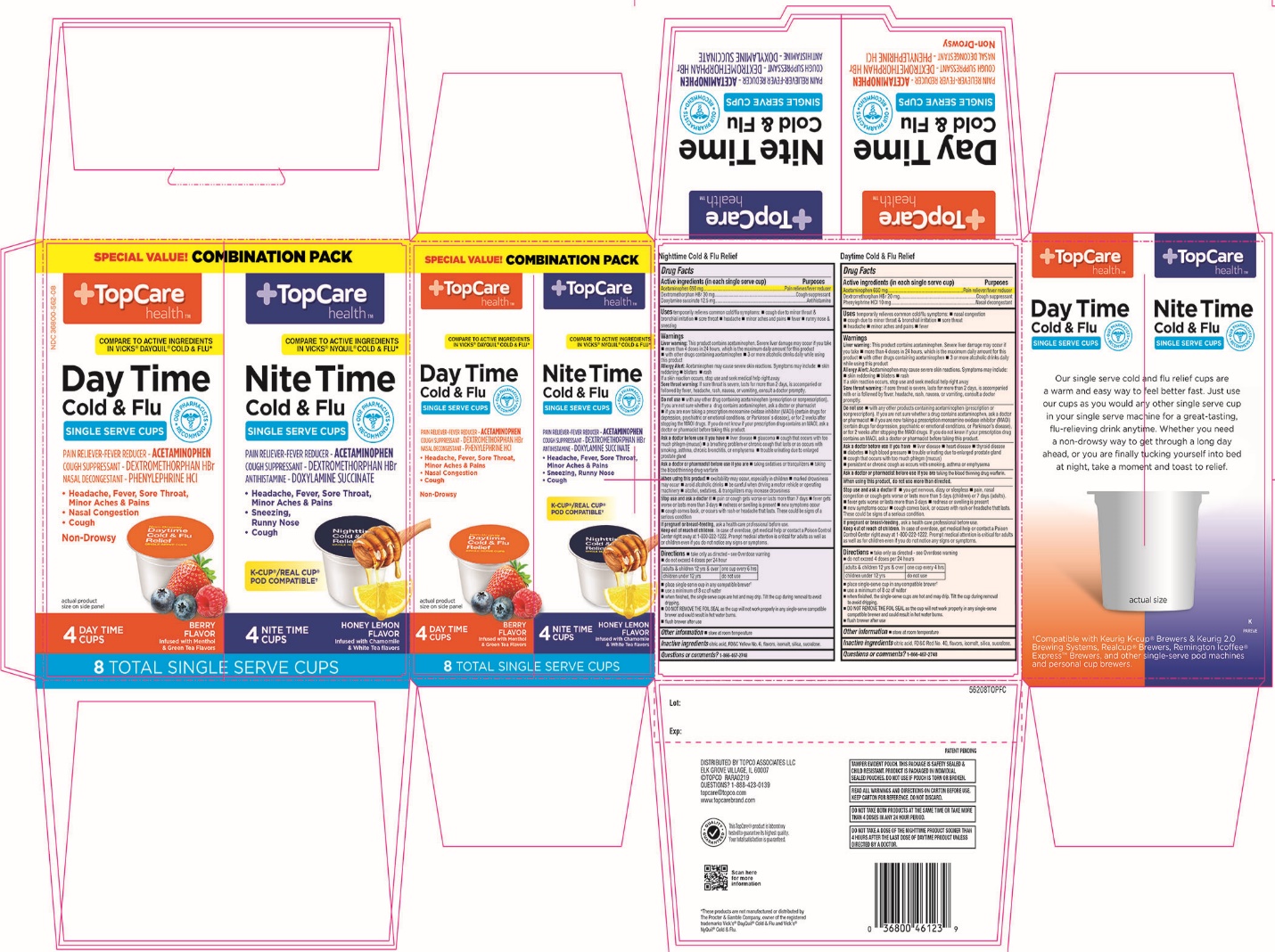 DRUG LABEL: TopCare Health Non Drowsy Daytime Cold and Flu Relief And Nighttime Cold and Flu Relief
NDC: 36800-562 | Form: KIT | Route: ORAL
Manufacturer: TopCare Health
Category: otc | Type: HUMAN OTC DRUG LABEL
Date: 20221130

ACTIVE INGREDIENTS: ACETAMINOPHEN 650 mg/1 1; DEXTROMETHORPHAN HYDROBROMIDE 20 mg/1 1; PHENYLEPHRINE HYDROCHLORIDE 10 mg/1 1; ACETAMINOPHEN 650 mg/1 1; DEXTROMETHORPHAN HYDROBROMIDE 30 mg/1 1; DOXYLAMINE SUCCINATE 12.5 mg/1 1
INACTIVE INGREDIENTS: ANHYDROUS CITRIC ACID; FD&C RED NO. 40; ISOMALT; SILICON DIOXIDE; SUCRALOSE; ANHYDROUS CITRIC ACID; FD&C YELLOW NO. 6; ISOMALT; SILICON DIOXIDE; SUCRALOSE

TopCare health™ Day and Night Combination Pack Non-Drowsy Daytime Cold and Flu Relief Single Serve Cups Nighttime Cold and Flu Relief Single Serve Cups

Drug Facts Daytime Cold & Flu Relief

ACTIVE INGREDIENT

PURPOSE

Active ingredients (in each single serve cup) | Purposes
Acetaminophen 650 mg | Pain reliever/fever reducer
Dextromethorphan HBr 20 mg | Cough suppressant
Phenylephrine HCl 10 mg | Nasal decongestant

Drug Facts Nighttime Cold & Flu Relief

Active ingredients (in each single serve cup) | Purposes
Acetaminophen 650 mg | Pain reliever/Fever reducer
Dextromethorphan HBr 30 mg | Cough suppressant
Doxylamine succinate 12.5 mg | Antihistamine

Uses

Daytime

temporarily relieves common cold/flu symptoms:

- nasal congestion
- cough due to minor throat & bronchial irritation
- sore throat
- headache
- minor aches & pains
- fever
Nighttime

temporarily relieves common cold/flu symptoms:

- cough due to minor throat & bronchial irritation
- sore throat
- headache
- minor aches & pains
- fever
- runny nose & sneezing

Warnings

Liver warning:

Daytime

This product contains acetaminophen.

Severe liver damage may occur if you take

- more than 4 doses in 24 hours, which is the maximum daily amount for this product
- with other drugs containing acetaminophen
- 3 or more alcoholic drinks daily while using this product

Allergy Alert: Acetaminophen may cause severe skin reaction. Symptom may include:

- Skin reddening
- Blisters
- Rash

If a skin reaction occurs, stop use and seek medical help right away.

Nighttime

This product contains acetaminophen.

Severe liver damage may occur if you take

- more than 4 doses in 24 hours, which is the maximum daily amount for this product
- with other drugs containing acetaminophen
- 3 or more alcoholic drinks every day while using this product

Allergy Alert: Acetaminophen may cause severe skin reaction. Symptom may include:

- Skin reddening
- Blisters
- Rash

If a skin reaction occurs, stop use and seek medical help right away.

Sore throat warning:

Daytime

If sore throat is severe, lasts for more than 2 days, is accompanied with or followed by fever, headache, rash, nausea, or vomiting, consult a doctor promptly.

Nighttime

If sore throat is severe, lasts for more than 2 days, is accompanied with or followed by fever, headache, rash, nausea, or vomiting, consult a doctor promptly.

Do not use

Daytime
Nighttime

- with any other products containing acetaminophen (prescription or nonprescription). If you are not sure whether a drug contains acetaminophen, ask a doctor or pharmacist.
- if you are now taking a prescription monoamine oxidase inhibitor (MAOI) (certain drugs for depression, psychiatric or emotional conditions, or Parkinson's disease), or for 2 weeks after stopping the MAOI drugs. If you do not know if your prescription drug contains an MAOI, ask a doctor or pharmacist before taking this product.
Nighttime

Ask a doctor before use if you have

Daytime

- liver disease
- heart disease
- thyroid disease
- diabetes
- high blood pressure
- trouble urinating due to enlarged prostate gland
- cough that occurs with too much phlegm (mucus)
- persistent or chronic cough such as occurs with smoking, asthma, or emphysema
Nighttime

Ask a doctor or pharmacist before use if you are

Daytime

taking the blood thinning drug warfarin.

Nighttime
taking sedatives or tranquilizers
taking the blood thinning drug warfarin

Daytime: When using this product, do not use more than directed.

Nighttime

- excitability may occur, especially in children
- marked drowsiness may occur
- avoid alcoholic drinks
- be careful when driving a motor vehicle or operating machinery
- alcohol, sedatives, & tranquilizers may increase drowsiness

Stop use and ask a doctor if

Daytime

- you get nervous, dizzy or sleepless
- pain, nasal congestion or cough gets worse or lasts more than 5 days(children) or 7 days(adults)
- fever gets worse or lasts more than 3 days
- redness or swelling is present
- new symptoms occur
- cough comes back, or occurs with rash or headache that lasts.

These could be signs of a serious condition.

Nighttime

- pain or cough gets worse or lasts more than 7 days
- fever gets worse or lasts more than 3 days
- redness or swelling is present
- new symptoms occur
- cough comes back, or occurs with rash or headache that lasts.

These could be signs of a serious condition.

PREGNANCY OR BREAST FEEDING

If pregnant or breast-feeding, ask a health care professional before use.

Keep out of reach of children.

Daytime

In case of overdose, get medical help or contact a Poison Control Center right away at 1-800-222-1222. Prompt medical attention is critical for adults as well as for children even if you do not notice any signs or symptoms.

Nighttime

In case of overdose, get medical help or contact a Poison Control Center right away at 1-800-222-1222. Prompt medical attention is critical for adults as well as for children even if you do not notice any signs or symptoms.

Directions

Daytime

- take only as directed - see Overdose warning
- do not exceed 4 doses per 24 hours

adults & children 12yrs & over | one cup every 4 hrs
children under 12yrs | do not use

- place single–serve cup in compatible brewer
- use a minimum of 8 oz of water
- when finished, the single serve cups are hot and may drip. Tilt the cup during removal to avoid dripping.
- DO NOT REMOVE THE FOIL SEAL as the cup will not work properly in any single serve compatible brewer and could result in hot water burns.
- Flush brewer after use
Nighttime

adults & children 12yrs & over | one cup every 6 hrs
children under 12yrs | do not use

- place single-serve cup in any compatible brewer†
- use a minimum of 8 oz of water
- when finished, the single serve cups are hot and may drip.
Tilt the cup during removal to avoid dripping.

Other information

Daytime

- store at room temperature
Nighttime

Inactive ingredients

Daytime

citric acid, FD&C Red No. 40, flavors, isomalt, silica, sucralose

Nighttime

citric acid, FD&C Yellow No.6, flavors, isomalt, silica, sucralose

Questions or comments?

Daytime

1-866-467-2748

Nighttime

1-866-467-2748

PRINCIPAL DISPLAY PANEL

DAY & NIGHT COMBINATION PACK

TopCare Health™

NDC 36800-562-08

COMPARE TO THE ACTIVE INGREDIENTS IN VICKS® DAYQUIL® COLD & FLU*

Non-Drowsy

Daytime

Cold & Flu Relief

Single serve

Cups

COMPATIBLE WITH KEURIG® K- CUP Brewers & Keurig 2.0 Brewing System, Realcup® Brewers, Remington Icoffe® Express™ Brewers and other single-serve pod machine and personal cup brewers,

Day Time Cold & Flu

Pain reliever/Fever reducer, ACETAMINOPHEN

Cough suppressant

DEXTROMETHORPHAN Habra

Nasal decongestant

PHENYLEPHRINE HCl

Relieves:

- Headache, fever, sore throat
- Minor aches & pains
- Nasal congestion
- Cough

Berry Flavor infused with Menthol & Green Tea Flavors

Naturally and Artificially Flavored

Alcohol free

4 DAYTIME CUPS

Compare to the active ingredients in Vicks® NyQuil®Cold & Flu*

Nighttime

Cold & Flu Relief
Single Serve Cups

K-CUP®/REAL CUP® POD COMPATIBLE

ACETAMINOPHEN

Pain reliever/Fever reducer

DEXTROMETHORPHAN HBr

Cough suppressant
DOXYLAMINE SUCCINATE

Antihistamine

Relieves:

- Headache, fever, sore throat
- Minor aches and pains
- Sneezing, runny Nose
- Cough
Honey Lemon Flavor Infused Chamomile & White Tea Flavors

4 NIGHTTIME CUPS

8 TOTAL SINGLE SERVE CUPS

Our single serve cold and flu relief cups are a warm and easy way to feel better fast. Just use our cups as you would any other single serve cup in your single serve machine for a great- tasting, flu-relieving drink anytime .Whether you need a non- drowsy way to get through a long day ahead ,or you are finally tucking yourself into bed at night, take a moment and toast to relief.

*This product is not manufactured or distributed by Procter and Gamble Company, owner of the registered trademark Vicks® DayQuil ®Cold & Flu and Vicks® NyQuil® Cold &Flu.

†COMPATIBLE WITH KEURIG® K- CUP® BREWERS & Keurig 2.0 BREWING SYSTEMS.

THIS PRODUCT IS NOT AFFILIATED WITH KEURIG, INC.

Distributed by: TOPCO ASSOCIATES LLC

ELK GROVE VILLAGE, IL 60007

©TOPCO RARA0219

QUESTIONS? 1-888-423-0139

topcare@topco.com

www.topcarebrand.com

Quality Guarantee

This TopCare product is laboratory tested to guarantee its highest quality. Your total satisfaction is guaranteed.

PATENT PENDING

TAMPER EVIDENT POUCH: THIS PACKAGE IS SAFETY SEALED & CHILD RESISTANT. PRODUCT IS PACKEGED IN INDIVIDUAL SEALED POUCHES. DO NOT USE IF SEALED CUP IS TORN AND BROKEN.

READ ALL WARNINGS AND DIRECTIONS ON CARTON BEFORE USE .KEEP CARTON FOR REFERENCE, DO NOT DISCARD.

DO NOT TAKE BOTH PRODUCTS AT THE SAME TIME OR TAKE MORE THAN 4 DOSES IN ANY 24 –HOUR PERIOD.

DO NOT TAKE A DOSE OF THE NIGHTTIME PRODUCT SOONER THAN 4 HOURS AFTER THE LAST DOSE OF DAYTIME PRODUCT UNLESS DIRECTED BY DOCTOR.